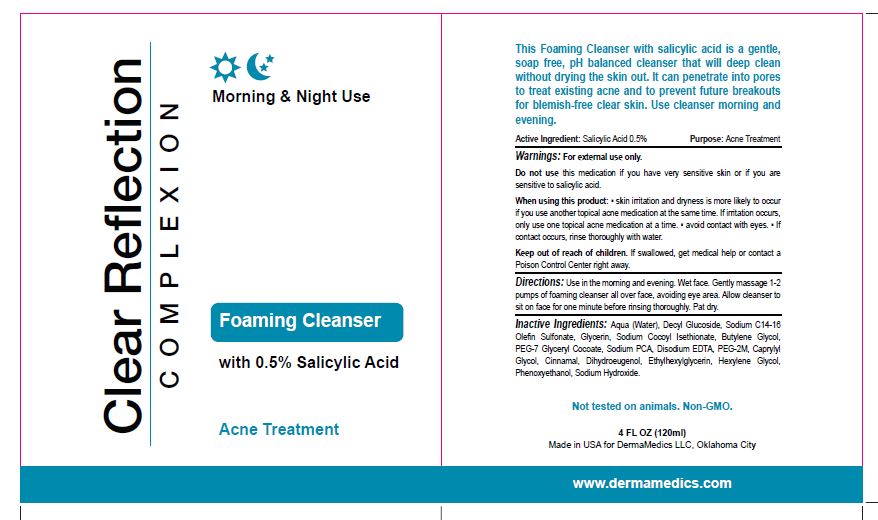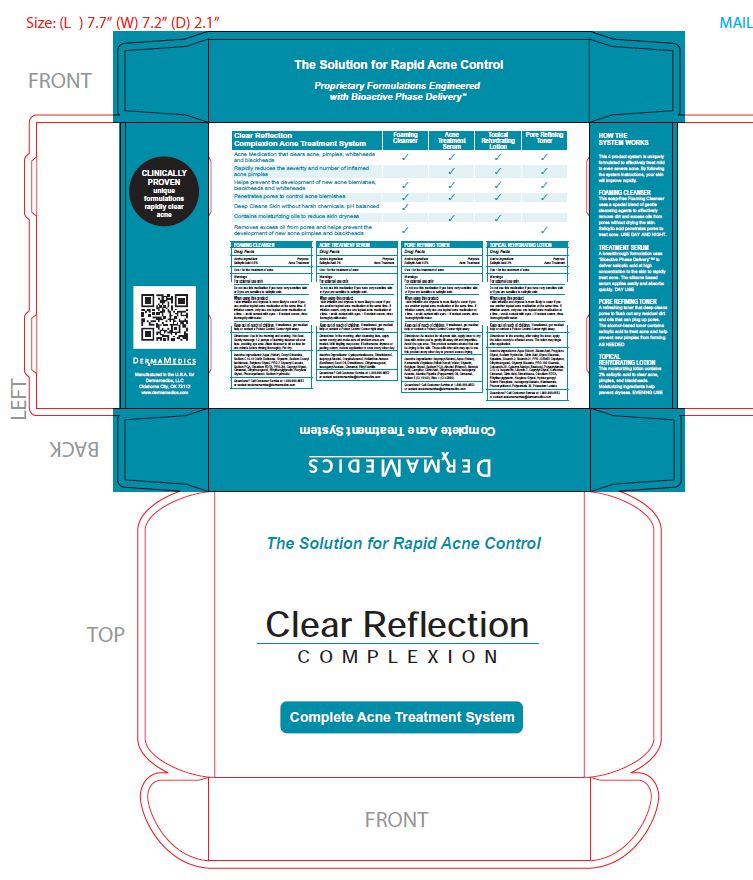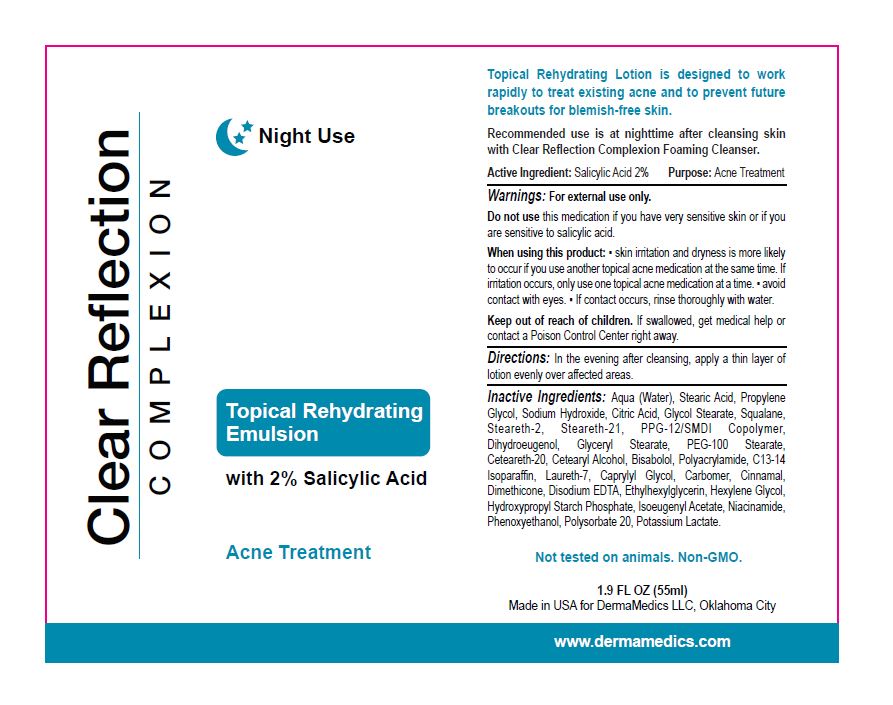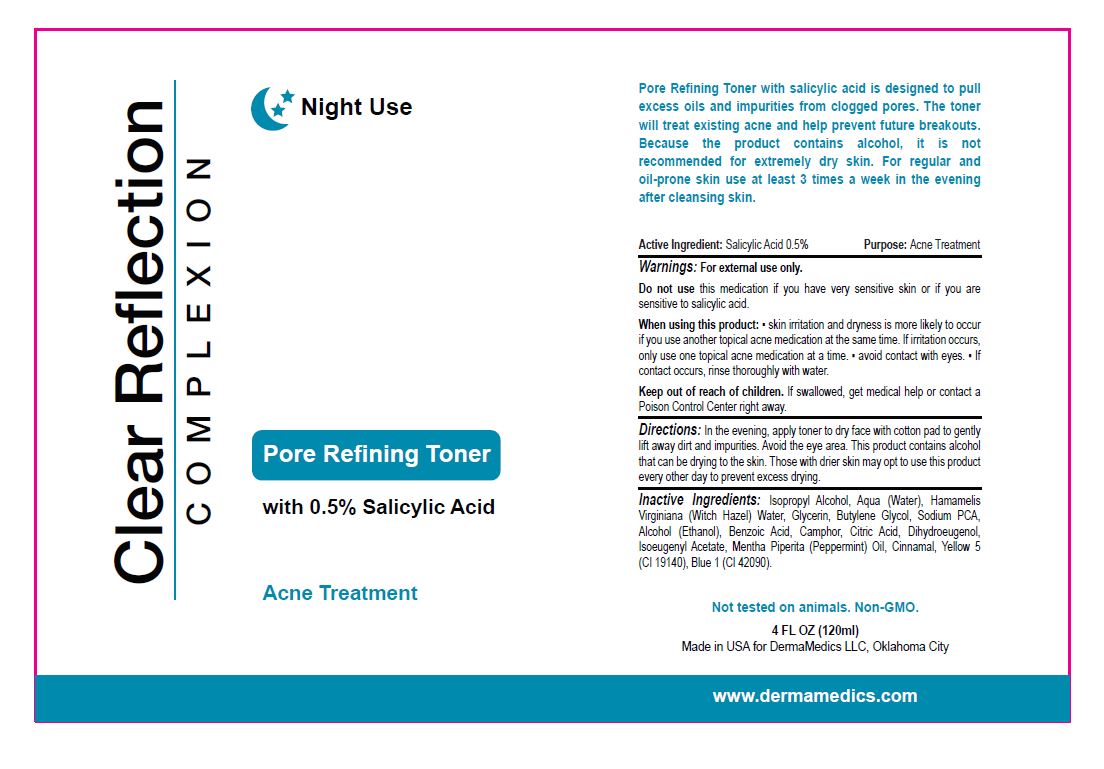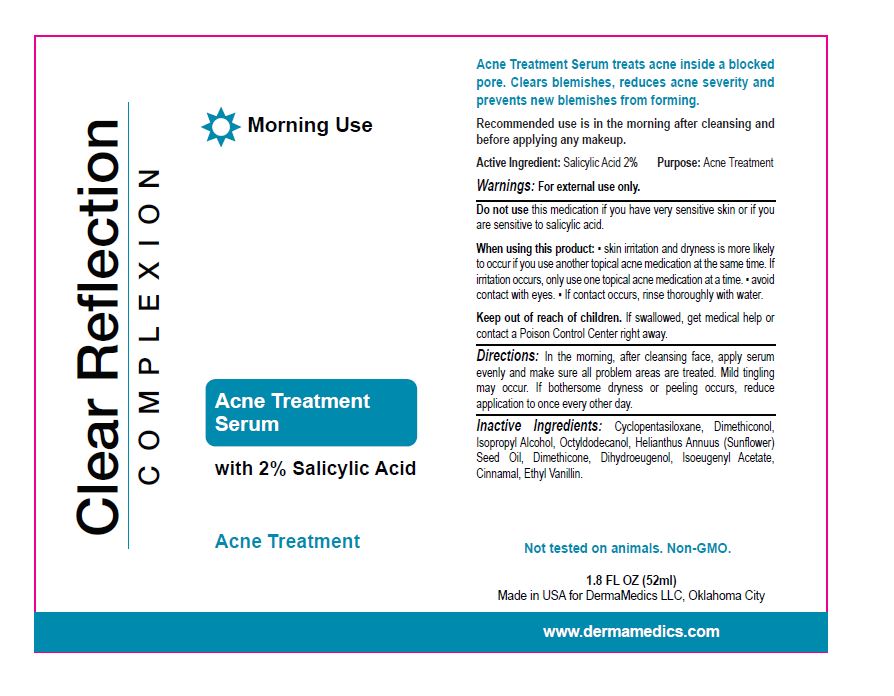 DRUG LABEL: Clear Reflection Complexion
NDC: 76348-710 | Form: KIT | Route: TOPICAL
Manufacturer: RENU LABORATORIES, INC.
Category: otc | Type: HUMAN OTC DRUG LABEL
Date: 20210819

ACTIVE INGREDIENTS: SALICYLIC ACID 0.56 g/112 g; SALICYLIC ACID 1 g/53 g; SALICYLIC ACID 0.56 g/112 g; SALICYLIC ACID 1 g/50 g
INACTIVE INGREDIENTS: DIHYDROEUGENOL; PEPPERMINT OIL; WITCH HAZEL; FD&C YELLOW NO. 5; BENZOIC ACID; ANHYDROUS CITRIC ACID; BUTYLENE GLYCOL; CAMPHOR (SYNTHETIC); WATER; ISOPROPYL ALCOHOL; ISOEUGENYL ACETATE; CINNAMALDEHYDE; FD&C BLUE NO. 1; GLYCERIN; SODIUM PYRROLIDONE CARBOXYLATE; GLYCOL STEARATE; .ALPHA.-BISABOLOL, (+)-; STEARETH-21; HYDROXYPROPYL CORN AMYLOPECTIN, PHOSPHATE CROSSLINKED (4000 MPA.S AT 5%); CARBOMER INTERPOLYMER TYPE A (55000 CPS); WATER; STEARIC ACID; DIHYDROEUGENOL; ISOEUGENYL ACETATE; CINNAMALDEHYDE; DIMETHICONE 500; PHENOXYETHANOL; CAPRYLYL GLYCOL; ETHYLHEXYLGLYCERIN; HEXYLENE GLYCOL; ANHYDROUS CITRIC ACID; PROPYLENE GLYCOL; POLYSORBATE 20; POLYOXYL 20 CETOSTEARYL ETHER; SQUALANE; STEARETH-2; PPG-12/SMDI COPOLYMER; POTASSIUM LACTATE, DL-; CETOSTEARYL ALCOHOL; EDETIC ACID; NIACINAMIDE; POLYETHYLENE GLYCOL 4500; DIHYDROEUGENOL; CINNAMALDEHYDE; WATER; SODIUM C14-16 OLEFIN SULFONATE; EDETATE DISODIUM; SODIUM PYRROLIDONE CARBOXYLATE; SODIUM HYDROXIDE; PHENOXYETHANOL; GLYCERIN; DECYL GLUCOSIDE; SODIUM COCOYL ISETHIONATE; BUTYLENE GLYCOL; POLYETHYLENE OXIDE 200000; CAPRYLYL GLYCOL; ETHYL VANILLIN; ISOEUGENYL ACETATE; CINNAMALDEHYDE; CYCLOMETHICONE 5; DIMETHICONE 12500; ISOPROPYL ALCOHOL; DIHYDROEUGENOL; DIMETHICONOL (50000 CST); SUNFLOWER OIL; OCTYLDODECANOL

Clear Reflection Complexion KIT

Active Ingredient:

Salicylic Acid 0.5 percent

PART 1 - CLEAR REFLECTION FOAMING CLEANSER

Salicylic Acid

0.5 percent

PART 2 - CLEAR REFLECTION COMPLEXION ACNE TREATMENT SERUM

2 percent Salicylic Acid

PART 3 - CLEAR REFLECTION COMPLEXION Pore Refining Toner

Active Ingredient

Salicylic Acid

PART 4 - CLEAR REFLECTION COMPLEXION Topical Rehydrating Emulsion

Active Ingredient

Salicylic Acid

Warnings

For external use only

PART 1 CLEANSER WARNING

For external use only.

PART 2 - ACNE TREATMENT SERUM Warnings:

For external use only.

PART 3 - CLEAR REFLECTION COMPLEXION Pore Refining Toner

For external use only.

PART 4

For external use only

Do not use this medication if you have very sensitive skin or if you are sensitive to salicylic acid.

PART 1 CLEANSER

Do not use this medication if you have very sensitive skin or if you are sensitive to salicylic acid.

PART 2 - ACNE TREATMENT SERUM

Do not use this medication if you have very sensitive skin or if you are sensitive to salicylic acid.

PART 3 - CLEAR REFLECTION COMPLEXION Pore Refining Toner

Do not use this medication if you have very sensitive skin or if you are sensitive to salicylic acid.

PART 4 - Clear Reflection COMPLEXION Topical Rehydrating Emulsion

Do not use this medication if you have very sensitive skin or if you are sensitive to salicylic acid.

When using this product

- skin irritation and dryness is more likely to occur if you use another topical acne medication at the same time. If irritation occurs, only use one topical acne medication at a time.
- avoid contact with eyes.
- If contact occurs, rinse thoroughly with water.

PART 2 - ACNE TREATMENT SERUM

Skin irritation and dryness is more likely to occur if you use another topical acne medication at the same time. If irritation occurs, only use one topical acne medication at a time

- avoid contact with eyes
- If contact occurs, rinse thoroughly with water.

PART 3 - Pore Refining Toner

When using this product

- skin irritation and dryness is more likely to occur if you use another topical acne medication at the same time. If irritation occurs, only use one topical acne medication at a time
- avoid contact with eyes
- if contact occurs, rinse thoroughly with water.

PART 1

When using this product

skin irritation and dryness is more likely to occur if you use another topical acne medication at the same time. If irritation occurs only use one topical acne medication at a time

avoid contact with eyes

if contact occurs rinse thoroughly with water

Keep out of reach of children. If swallowed, get medical help or contact a Poison Control Center right away.

PART 3 - Pore Refining Toner

Keep out of reach of children.

If swallowed get medical help or contact a Poison Control Center right away.

Part 4 - Topical Rehydrating Emulsion

Keep out of reach of children. If swallowed, get medical help or contact a Poison Control Center right away.

PART 1

Keep out of reach of children

If swallowed get medical help or contact a Poison Control Center right away

PART 2

Keep out of reach of children.

If swallowed get medical help or contact a Poison Control Center right away.

Directions

PART 1 - FOAMING CLEANSER - DIRECTIONS

Use in the morning and evening. Wet face. Gently massage 1-2 pumps of foaming cleanser all over face, avoiding eye area.

PART 3 - Pore Refining Toner

Directions

In the evening, apply toner to dry face with cotton pad to gently lift away dirt and impurities. Avoid the eye area. This product contains alcohol that can be drying to the skin. Those with drier skin may opt to use this product every other day to prevent excess drying.

PART 4 - Topical Rehydrating Emulsion

Recommended use is at nightime after cleansing skin with Clear Reflection Complexion Foaming Cleanser.

PART 2

Directions

In the morning, after cleansing face, apply serum evenly and make sure all problem areas are treated. Mild tingling may occur. If bothersome dryness or peeling occurs, reduce application to once every other day.

Inactive Ingredients

Aqua (Water), Decyl Glucoside, Sodium C14-16 Olefin Sulfonate, Glycerin, Sodium Cocoyl Isethionate, Butylene Glycol, PEG-7 Glyceryl Cocoate, Sodium PCA, Disodium EDTA, PEG-5m, Caprylyl Glycol, Cinnamal, Dihydroeugenol, Ethylhexylglycerin, Hexylene Glycol, Phenoxyethanol, Sodium Hydroxide.

PART 1 - FOAMING CLEANSER INACTIVES

Aqua (Water), Decyl Glucoside, Sodium C14-16 Olefin Sulfonate, Glycerin, Sodium Cocoyl Isethionate, Butylene Glycol, PEG-7 Glyceryl Cocoate, Sodium PCA, Disodium EDTA, PEG-5M, Caprylyl Glycol, Cinnamal, Dihydroeugenol, Ethylhexylglycerin, Hexylene Glycol, Phenoxyethanol, Sodium Hydroxide.

PART 2 - ACNE TREATMENT SERUM

Cyclopentasiloxane, Dimethiconol, Isopropyl Alcohol, Octyldodecanol, Helianthus Annuus (Sunflower) Seed Oil, Dimethicone, Dihydroeugenol, Isoeugenyl Acetate, Cinnamal, Ethyl Vanillin.

PART 3 - Pore Refining Toner

Isopropyl Alcohol, Aqua (Water), Hamamelis Virginiana (Witch Hazel), Glycerin, Butylene Glycol, Sodium PCA, Benzoic Acid, Camphor, Citric Acid, Dihydroeugenol, Isoeugenyl Acetate, Peppermint Oil, Cinnamal, Yellow 5 (CI 19140), Blue 1 (CI 42090).

PART 4 - Topical Rehydrating Emulsion

Inactive Ingredients:

Aqua (Water), Stearic Acid, Propylene Glycol, Sodium Hydroxide, Citric Acid, Glycol Stearate, Squalane, Steareth-2, Steareth-21, PPG-12/SMDI Copolymer, Dihydroeugenol, Glyceryl Stearate, PEG-100 Stearate, Ceteareth-20, Cetearyl Alcohol, Bisabolol, Polyacrylamide, C13-14 Isoparaffin, Laureth-7, Caprylyl Glycol, Carbomer, Cinnamal, Dimethicone, Disodium EDTA, Ethylhexylglycerin, Hexylene Glycol, Hydroxypropyl Starch Phosphate, Isoeugenyl Acetate, Niacinamide, Phenoxyethanol, Polysorbate 20, Potassium Lactate.

PURPOSE

Acne Treatment

PART 2 - Acne Treatment Serum

Purpose: Acne Treatment

PART 4

Purpose

Acne Treatment

PART 3

Purpose

Acne Treatment

PART 1

Acne Treatment

RECENT MAJOR CHANGES

The only change here was the bolding of a few words.

Not substantive.

No major changes occured.

Only date changed.

Dosage and Administration - no major change

Simple retyping to avoid copy and paste function.

INDICATIONS AND USAGE

see individual parts

PART 1 FOAMING CLEANSER

Use cleanser morning and evening

PART 2 ACNE TREATMENT SERUM

Recommended use is in the morning after cleansing and before applying any makeup.

part 3 Pore Refining Toner

For regular and oil-prone skin use at least 3 times a week in the evening after cleansing skin.

PART 4 Topical Rehydrating Emulsion

Recommended use is at nightime after cleansing

QUESTIONS

Call Customer Service at 1 800 990 6552 or contact customerservice@dermamedics.com

PACKAGE LABEL

ART FOR ENTIRE 4 PART KIT

PART 4 - CLEAR REFLECTION TOPICAL REHYDRATING EMULSION